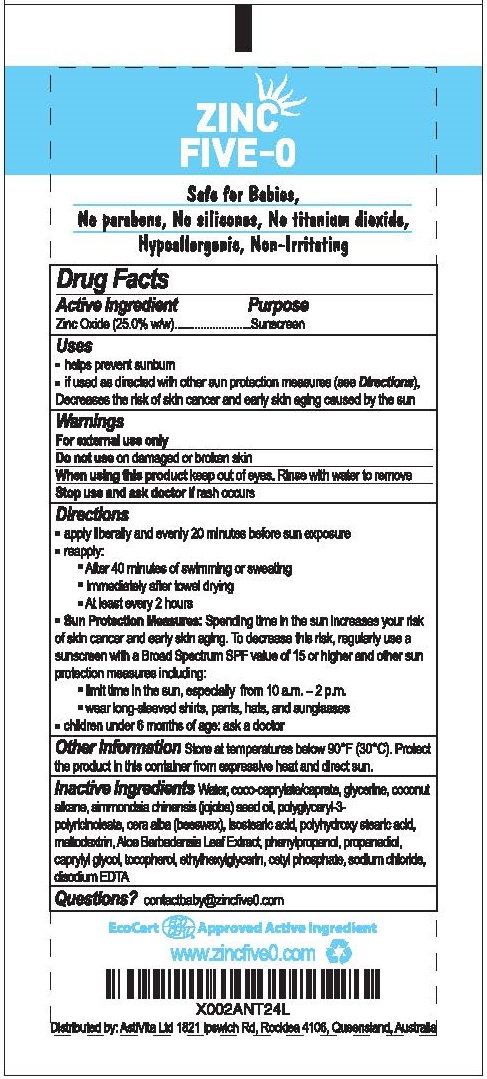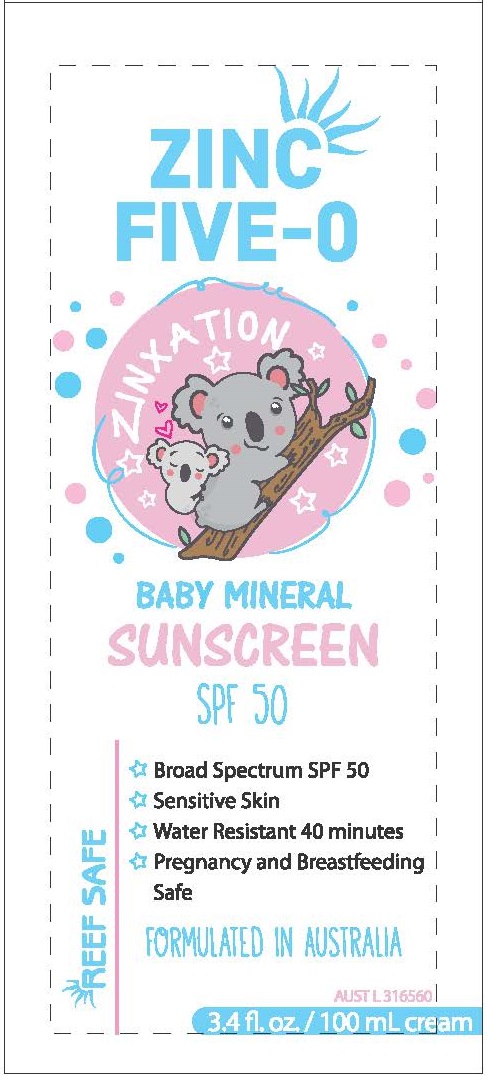 DRUG LABEL: ZINC FIVE-O ZINXATION BABY MINERAL SUNSCREEN
NDC: 80982-005 | Form: LOTION
Manufacturer: ASTIVITA LIMITED
Category: otc | Type: HUMAN OTC DRUG LABEL
Date: 20220127

ACTIVE INGREDIENTS: ZINC OXIDE 25 g/120 g
INACTIVE INGREDIENTS: WATER; COCO-CAPRYLATE/CAPRATE; GLYCERIN; COCONUT ALKANES; JOJOBA OIL; POLYGLYCERYL-3 RICINOLEATE; YELLOW WAX; ISOSTEARIC ACID; POLYHYDROXYSTEARIC ACID (2300 MW); MALTODEXTRIN; ALOE VERA LEAF; PHENYLPROPANOL; PROPANEDIOL; CAPRYLYL GLYCOL; TOCOPHEROL; ETHYLHEXYLGLYCERIN; CETYL PHOSPHATE; SODIUM CHLORIDE; EDETATE DISODIUM

ZINC FIVE-O ZINXATION BABY MINERAL SUNSCREEN SPF-50

ACTIVE INGREDIENT

ZINC OXIDE 25%

PURPOSE

SUNSCREEN

USES

- Helps prevent sunburn
- If used as directed with other sun protection measures (see Directions), decreased the risk of skin cancer and early skin aging caused by the sun

WARNINGS

FOR EXTERNAL USE ONLY.

DO NOT USE ON DAMAGED OR BROKEN SKIN.

WHEN USING THIS PRODUCT KEEP OUT OF EYES. RINSE WITH WATER TO REMOVE.

STOP USE AND ASK A DOCTOR IF RASH OCCURS.

DIRECTIONS:

- APPLY LIBERALLY AND EVENLY 20 MINUTES BEFORE SUN EXPOSURE
- REAPPLY:
- AFTER 40 MINUTES OF SWIMMING OR SWEATING
- IMMEDIATELY AFTER TOWEL DRYING
- AT LEAST EVERY 2 HOURS

- SUN PROTECTION MEASURES: SPENDING TIME IN THE SUN INCREASES YOUR RISK OF SKIN CANCER AND EARLY SKIN AGING. TO DECREASE THIS RISK, REGULARLY USE A SUNSCREEN WITH A BROAD SPECTRUM SPF VALUE OF 15 OR HIGHER AND OTHER SUN PROTECTION MEASURES INCLUDING:
- LIMIT TIME IN THE SUN, ESPECIALLY FROM 10 A.M. - 2 P.M.
- WEAR LONG-SLEEVED SHIRTS, PANTS, HATS, AND SUNGLASSES
- CHILDREN UNDER 6 MONTHS OF AGE: ASK A DOCTOR

OTHER INFORMATION

STORE AT TEMPERATURES BELOW 90°F (30°C). PROTECT THE PRODUCT IN THIS CONTAINER FROM EXCESSIVE HEAT AND DIRECT SUN.

INACTIVE INGREDIENTS

Water, Coco-caprylate/caprate, glycerine, coconut alkane, simmondsia chinensis (jojoba) seed oil, polyglyceryl-3-polyricinoleate, cera alba (beeswax), isostearic acid, polyhydroxy stearic acid, maltodextrin, Aloe Barbadensis Leaf Extract, phenylpropanol, propanediol, caprylyl glycol, tocopherol, ethylhexylglycerin, cetyl phosphate, sodium chloride, disodium EDTA

QUESTIONS?

contactbaby@zincfive0.com